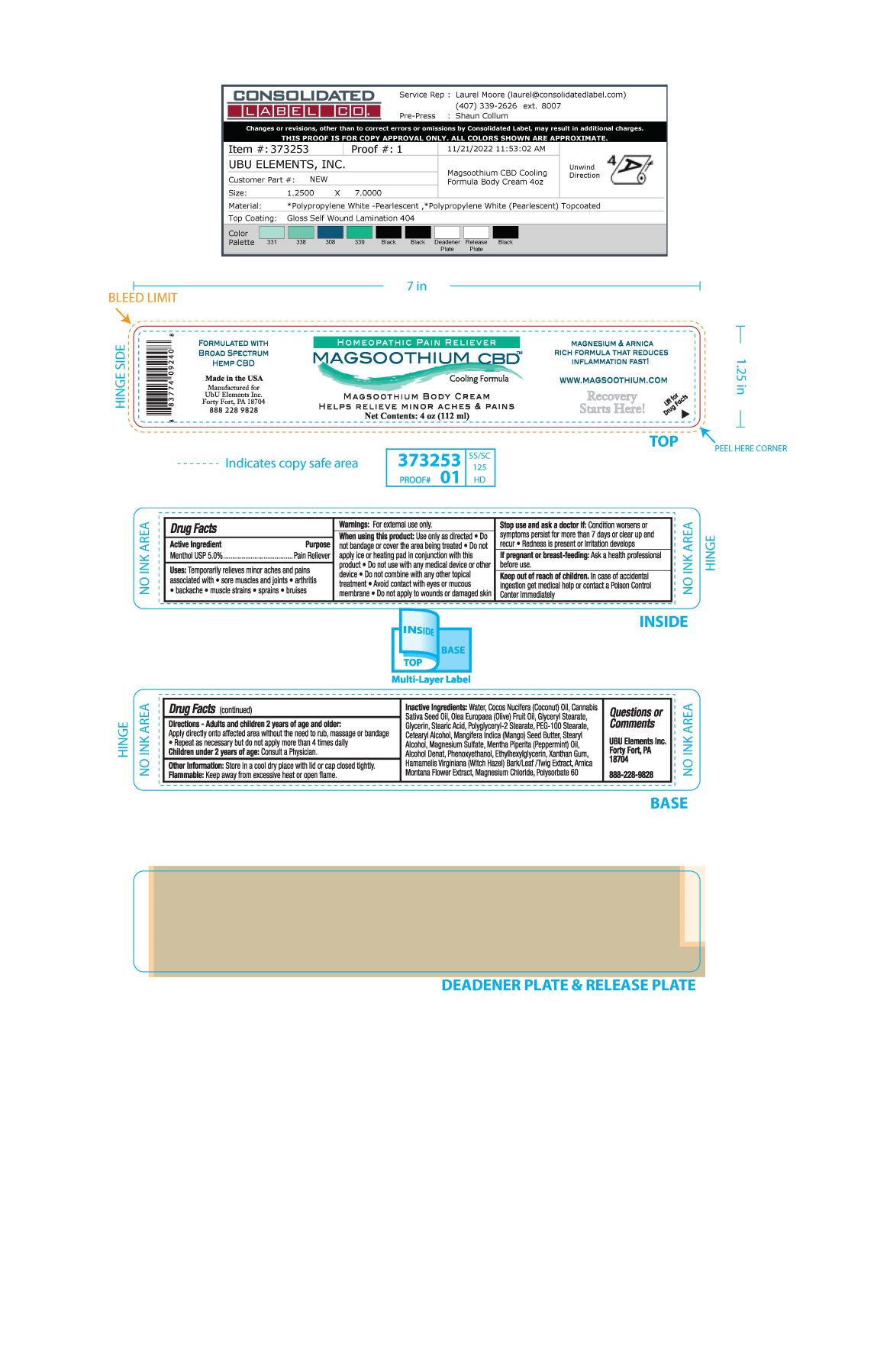 DRUG LABEL: Magsoothium Body Cooling Formula
NDC: 83262-002 | Form: CREAM
Manufacturer: Ubu/Elements, Inc.
Category: otc | Type: HUMAN OTC DRUG LABEL
Date: 20251216

ACTIVE INGREDIENTS: MENTHOL 5 g/100 mL
INACTIVE INGREDIENTS: ALCOHOL; MAGNESIUM SULFATE, UNSPECIFIED; MAGNESIUM CHLORIDE; ARNICA MONTANA FLOWER; CETOSTEARYL ALCOHOL; WATER; CANNABIS SATIVA SEED OIL; OLIVE OIL; COCONUT OIL; PEPPERMINT OIL; PHENOXYETHANOL; ETHYLHEXYLGLYCERIN; MANGIFERA INDICA SEED BUTTER; POLYGLYCERYL-2 STEARATE; STEARIC ACID; PEG-100 STEARATE; XANTHAN GUM; GLYCERIN; GLYCERYL MONOSTEARATE; STEARYL ALCOHOL; HAMAMELIS VIRGINIANA LEAF; POLYSORBATE 60

Magsoothium Body Cream Cooling Formula

Active Ingredient

Menthol USP 5.0%

Purpose
Topical Analgesic

PURPOSE

Uses Temporary relieves minor aches and pains associated with

- Sore muscles and joints
- arthritis
- backache
- muscle strains
- sprains
- bruises

Keep out of reach of children. In case of accidental ingestion get medical help or contact a Poison Control Center immediately

Stop use and ask a doctor if Condition worsens or symptoms persist for more than 7 days or clear up and recur

Redness is present or irritation develops

Warnings For external use only

When using this product use only as directed

- Do not bandage or cover the area being treated
- Do not apply ice or heating pad in conjunction with this product.
- Do not use with any medical device or other device
- Do not combine with any other topical treatment
- Avoid contact with eyes or mucous membrane
- Do not apply to wounds or damaged skin

If pregnant or breast-feeding Ask a health professional before use

DOSAGE AND ADMINISTRATION

Directions - Adults and children 2 years of age and older

Apply directly onto affected area without the need to rub, massage or bandage

- repeat as necessary but do not apply more than 4 times daily

Children under 2 years of age Consult a physician

INACTIVE INGREDIENT

Inactive Ingredients Water, Cocos Nucifera (Coconut) Oil, Cannabis Sativa Seed Oil, Olea Europaea (Olive) Fruit Oil, Glyceryl Stearate, Glycerin, Polyglyceryl-2 Stearate, PEG-100 Stearate, Cetearyl Acohol, Mangifera indica (Mango) Seed Butter, Stearyl Alcohol, Magnesium Sulfate, Mentha Piperita (Peppermint) Oil, Alcohol Denat., Phenoxyethanol,

Ethylhexylglycerin, Xanthan Gum, Hamamelis Virginiana (Witch Hazel) Bark/Leaf/Twig Extract, Arnica Montana Flower Extract, Magnesium Chloride, Polysorbate 60

PACKAGE LABEL

Homeopathic Pain Reliever

Magsoothium CBD Cooling Formula

Magsoothium Body Cream

Helps relieve minor aches & pains

Net Contents: 4 oz (112 ml)